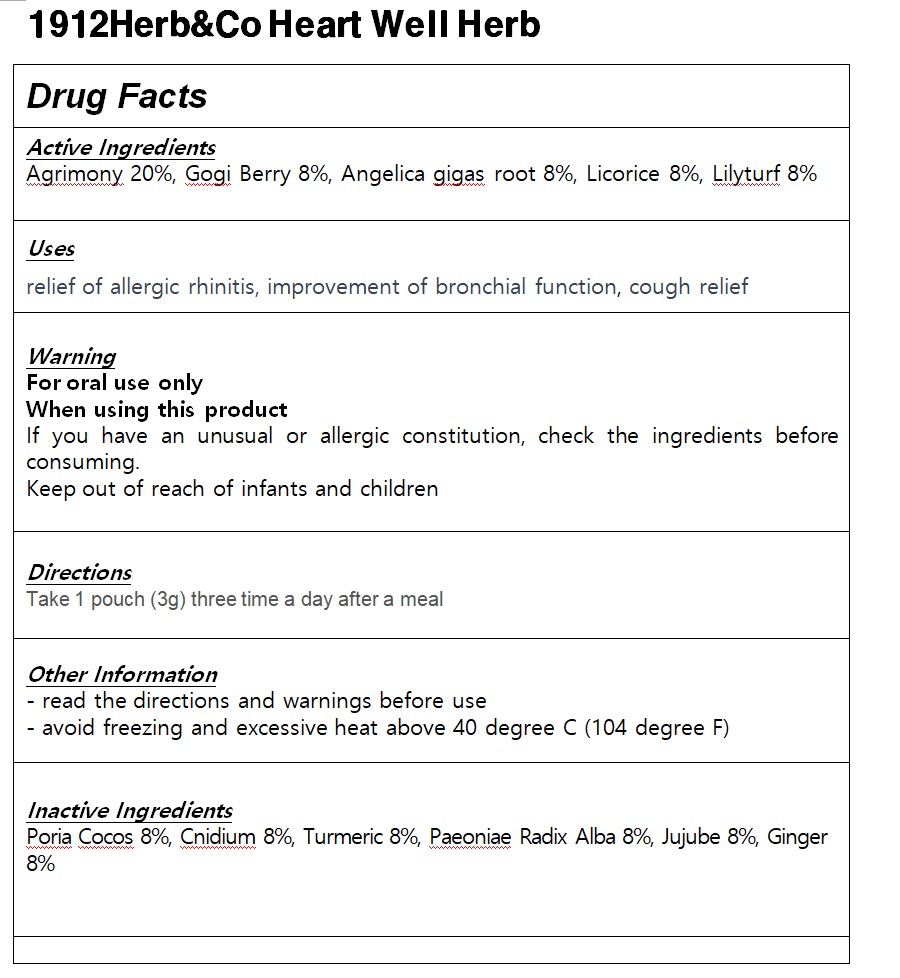 DRUG LABEL: 1912Herb Co Heart Well Herb
NDC: 83933-0003 | Form: POWDER
Manufacturer: Agricultural Corporation YUBIMUHUAN CO Ltd
Category: otc | Type: HUMAN OTC DRUG LABEL
Date: 20241110

ACTIVE INGREDIENTS: AGRIMONIA EUPATORIA 20 g/100 g
INACTIVE INGREDIENTS: PAEONIA LACTIFLORA ROOT

Drug Facts

ACTIVE INGREDIENT

Agrimony 20%, Gogi Berry 8%, Angelica gigas root 8%, Licorice 8%, Lilyturf 8%

INACTIVE INGREDIENT

Poria Cocos 8%, Cnidium 8%, Turmeric 8%, Paeoniae Radix Alba 8%, Jujube 8%, Ginger 8%

PURPOSE

digestive enhancement, relief of stomach pain, improvement of digestive function

keep out of reach of the children

INDICATIONS AND USAGE

Take 1 pouch (3g) three time a day after a meal

WARNINGS

If you have an unusual or allergic constitution, check the ingredients before consuming.

DOSAGE AND ADMINISTRATION

for oral use only